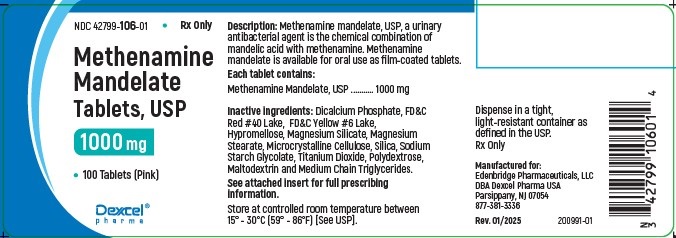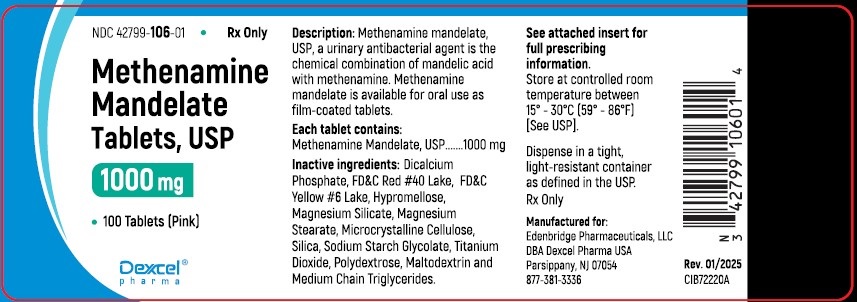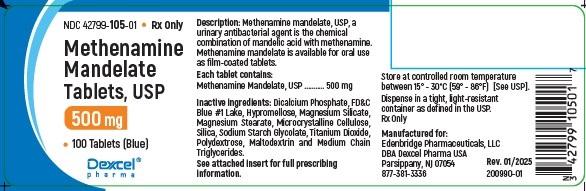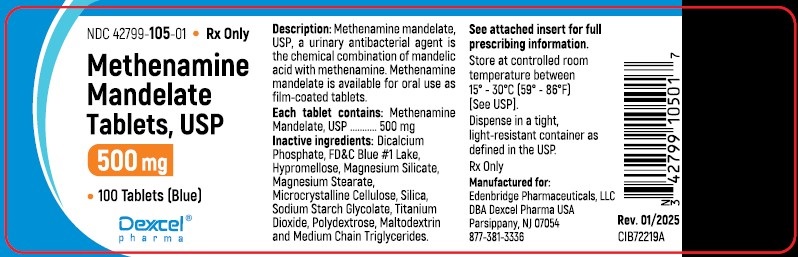 DRUG LABEL: Methenamine Mandelate
NDC: 42799-106 | Form: TABLET
Manufacturer: Edenbridge Pharmaceuticals LLC.
Category: prescription | Type: Human Prescription Drug Label
Date: 20260122

ACTIVE INGREDIENTS: METHENAMINE MANDELATE 1000 mg/1 1
INACTIVE INGREDIENTS: CALCIUM PHOSPHATE, DIBASIC, ANHYDROUS; HYPROMELLOSES; MAGNESIUM STEARATE; MAGNESIUM ALUMINUM SILICATE; CELLULOSE, MICROCRYSTALLINE; SILICON DIOXIDE; SODIUM STARCH GLYCOLATE TYPE A POTATO; TITANIUM DIOXIDE; FD&C RED NO. 40; FD&C YELLOW NO. 6; POLYDEXTROSE; MALTODEXTRIN; MEDIUM-CHAIN TRIGLYCERIDES

Methenamine Mandelate

DESCRIPTION:

Methenamine mandelate, USP, a urinary antibacterial agent, is the chemical combination of mandelic acid with methenamine. Methenamine mandelate, USP is available for oral use as film-coated tablets.

Active Ingredients:
Methenamine Mandelate: 500 mg or 0.5 gm.
Methenamine Mandelate: 1000 mg or 1.0 gm.

Other Ingredients: Dicalcium Phosphate, FD and C Blue #1 Lake, FD and C Red #40 Lake, FD and C Yellow #6 Lake, Hypromellose, Magnesium Silicate, Magnesium Stearate, Microcrystalline Cellulose, Silica, Sodium Starch Glycolate, Titanium Dioxide, Polydextrose, Maltodextrin, and Medium Chain Triglycercides.

CLINICAL PHARMACOLOGY

Methenamine mandelate, USP is readily absorbed but remains essentially inactive until it is excreted by the kidney and concentrated in the urine. An acid urine is essential for antibacterial action, with maximum efficacy occurring at pH 5.5 or less. In an acid urine, mandelic acid exerts its antibacterial action and also contributes to the acidification of the urine. Mandelic acid is excreted both by glomerular filtration and tubular excretion. The methenamine component, in an acid urine, is hydrolyzed to ammonia and to the bactericidal agent formaldehyde. There is equally effective antibacterial activity against both gram-positive and gram-negative organisms, since the antibacterial action of mandelic acid and formaldehyde is nonspecific. There are reports that methenamine mandelate, USP is ineffective in some infections with Proteus vulgaris and urea-splitting strains of Pseudomonas aeruginosa and A aerogenes. Since urea-splitting strains may raise the pH of the urine, particular attention to supplementary acidification is required. However, results in any single case will depend to a large extent on the underlying pathology and the overall management.

INDICATIONS AND USAGE

Methenamine mandelate, USP is indicated for the suppression or elimination of bacteriuria associated with pyelonephritis, cystitis, and other chronic urinary tract infections; also for infected residual urine sometimes accompanying neurologic diseases. When used as recommended, methenamine mandelate, USP is particularly suitable for long-term therapy because of its safety and because resistance to the nonspecific bactericidal action of formaldehyde does not develop. Pathogens resistant to other antibacterial agents may respond to methenamine mandelate, USP because of the nonspecific effect of formaldehyde formed in an acid urine.

Prophylactic Use Rationale: Urine is a good culture medium for many urinary pathogens. Inoculation by a few organisms (relapse or reinfection) may lead to bacteriuria in susceptible individuals. Thus, the rationale of management in recurring urinary tract infection (bacteriuria) is to change the urine from a growth-supporting to a growth-inhibiting medium. There is a growing body of evidence that long-term administration of methenamine mandelate, USP can prevent the recurrence of bacteriuria in patients with chronic pyelonephritis.

Therapeutic Use Rationale: Methenamine mandelate, USP helps to sterilize the urine, and in some situations in which underlying pathologic conditions prevent sterilization by any means, it can help to suppress the bacteriuria. Methenamine mandelate, USP should not be used alone for acute infections with parenchymal involvement causing systemic symptoms such as chills and fever. A thorough diagnostic investigation as a part of the overall management of the urinary tract infection should accompany the use of methenamine mandelate, USP.

CONTRAINDICATIONS

Contraindicated in renal insufficiency.

Methenamine mandelate, USP should not be used in patients who have previously exhibited hypersensitivity to it.

PRECAUTIONS

GENERAL PRECAUTIONS

Dysuria may occur (usually at higher than recommended dosage). This can be controlled by reducing the dosage and the acidification. When urine acidification is contraindicated or unattainable (as with some urea-splitting bacteria), the drug is not recommended.

DRUG INTERACTIONS

Formaldehyde and sulfamethizole form an insoluble precipitate in acid urine; therefore, methenamine mandelate, USP should not be administered concurrently with sulfamethizole.

DRUG & OR LABORATORY TEST INTERACTIONS

Formaldehyde interferes with fluorometric procedures for determination of urinary catecholamines and vanillylmandelic acid (VMA), causing erroneously high results. Formaldehyde also causes falsely decreased urine estriol levels by reacting with estriol when acid hydrolysis techniques are used; estriol determinations which use enzymatic hydrolysis are unaffected by formaldehyde. Formaldehyde causes falsely elevated 17-hydroxycorticosteroid levels when the Porter-Silber method is used and falsely decreased 5-hydroxyindoleacetic acid (5HIAA) levels by inhibiting color development when nitrosonaphthol methods are used.

PREGNANCY

Pregnancy Category C: Animal reproduction studies have not been conducted with methenamine mandelate, USP. It is also not known whether methenamine mandelate, USP can cause fetal harm when administered to a pregnant woman or can affect reproduction capacity. Methenamine mandelate, USP should be given to a pregnant woman only if clearly needed. Since introduction, published reports on the use of methenamine mandelate, USP in pregnant women have not shown an increased risk of fetal abnormalities from use during pregnancy.

ADVERSE REACTIONS

An occasional patient may experience gastrointestinal disturbance or a generalized skin rash. Microscopic and rarely gross hematuria have been described.

DOSAGE AND ADMINISTRATION

The average adult dose is 4 grams daily given as 1 gram after each meal and at bedtime. Children 6 to 12 should receive half the adult dose, and children under 6 years of age should receive 250 mg per 30 lb body weight, four times daily. (See chart) Since an acid urine is essential for antibacterial activity, with maximum efficacy occurring at pH 5.5 or below, restriction of alkalinizing foods and medication is thus desirable. If testing of urine pH reveals the need, supplemental acidification should be given.

Dosages
Dosage | Adults | Pediatric Patients
 | Tablets | Tablets
1000mg | 1 tablet qid | -
500mg | 2 tablets qid | (Ages 6-12) 1 tablet qid

HOW SUPPLIED

Methenamine Mandelate Tablets, USP 500 mg are supplied as:
NDC 42799-105-01 Bottles of 100
Each tablet is blue, film coated, and bears the product code “105”.

Methenamine Mandelate Tablets, USP 1000 mg are supplied as:
NDC 42799-106-01 Bottles of 100
Each tablet is pink, film coated, and bears the product code “106”.

Store at controlled room temperature between 15°-30°C (59°-86°F)[See USP].
Dispense in a tight, light-resistant container as defined in the USP.

Manufactured for:
Edenbridge Pharmaceuticals, LLC

DBA Dexcel Pharma USA
Parsippany, NJ 07054
877-381-3336

Rev.01/2025